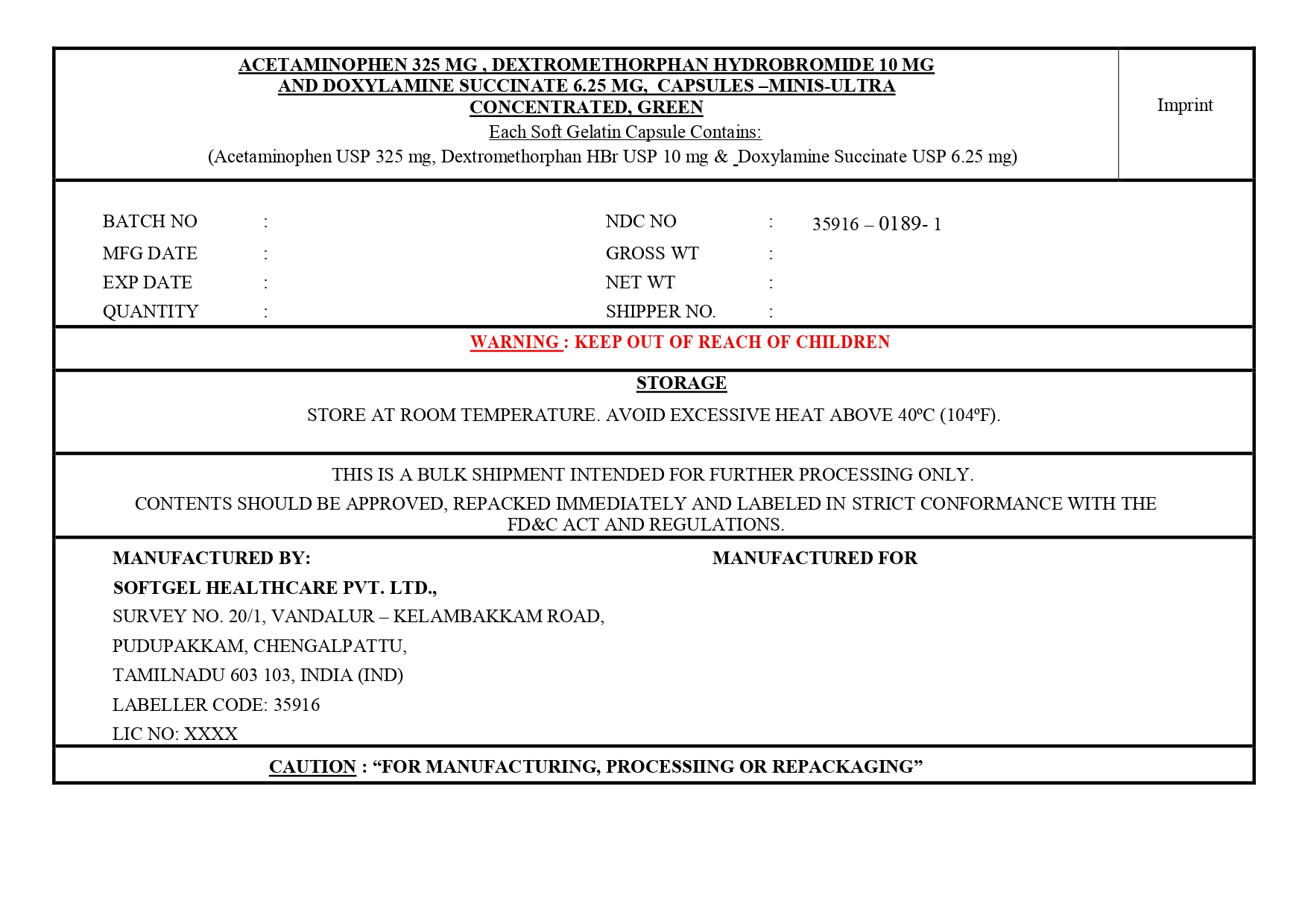 DRUG LABEL: Acetaminophen, Dextromethorphan Hydrobromide and Doxylamine Succinate
NDC: 35916-0189 | Form: CAPSULE, LIQUID FILLED
Manufacturer: SOFTGEL HEALTHCARE PRIVATE LIMITED
Category: otc | Type: HUMAN OTC DRUG LABEL
Date: 20260127

ACTIVE INGREDIENTS: ACETAMINOPHEN 325 mg/1 1; DEXTROMETHORPHAN HYDROBROMIDE 10 mg/1 1; DOXYLAMINE SUCCINATE 6.25 mg/1 1
INACTIVE INGREDIENTS: FD&C BLUE NO. 1; 1,4-SORBITAN; MICA; POLYETHYLENE GLYCOL 400; POVIDONE K30; D&C YELLOW NO. 10; SORBITOL; GLYCERIN; GELATIN; TITANIUM DIOXIDE; WATER

Acetaminophen 325mg, Dextromethorphan Hydrobromide 10mg & Doxylamine Succinate 6.25 mg Capsules (Minis, Ultra-concentrated, Green)

Active Ingredients (in each capsule)

Acetaminophen USP 325 mg
Dextromethorphan HBr USP 10 mg
Doxylamine Succinate USP 6.25 mg

Purposes

Pain reliever/fever reducer

Cough suppressant

Antihistamine

Uses

• temporarily relieves these symptoms due to a cold or flu :

• minor aches and pains • headache • cough

• sore throat • nasal and sinus congestion

• temporarily reduces fever

Warnings

Liver warning: This product contains acetaminophen. Severe liver damage may occur if you take

• more than 4,000 mg of acetaminophen in 24 hours

• with other drugs containing acetaminophen

• 3 or more alcoholic drinks every day while using this product

Allergy alert: Acetaminophen may cause severe skin or severe allergic reactions. Symptoms may include:

• skin reddening • blisters • rash • hives

• facial swelling • asthma (wheezing) • shock

If a skin or general allergic reaction occurs, stop use and seek medical help right away

Sore throat warning: If sore throat is severe, persists for more than 2 days, is accompanied or followed by fever, headache, rash, nausea, or vomiting, consult a doctor promptly.

Do not use

• with any other drug containing acetaminophen (prescription or nonprescription). If you are not sure whether a drug contains acetaminophen, ask a doctor or pharmacist.

• if you are now taking a prescription monoamine oxidase inhibitor (MAOI) (certain drugs for depression, psychiatric, or emotional conditions, or Parkinson's disease), or for 2 weeks after stopping the MAOI drug. If you do not know if your prescription drug contains an MAOI, ask a doctor or pharmacist before taking this product.

• if you have ever had an allergic reaction to this product or any of its ingredients

• in children under 12 years of age

Ask a doctor before use if you have

• liver disease • heart disease • high blood pressure

• thyroid disease • diabetes

• cough that occurs with excessive phlegm (mucus)

• difficulty in urination due to enlargement of the prostate gland

• persistent or chronic cough such as occurs with smoking, asthma, or emphysema

Ask a doctor or pharmacist before use if you are taking the blood thinning drug warfarin

When using this product do not exceed recommended dosage

Stop use and ask a doctor if

• pain, cough, or nasal congestion gets worse or lasts more than 7 days
• fever gets worse or lasts more than 3 days
• redness or swelling is present
• new symptoms occur

• cough comes back or occurs with rash or headache that lasts.

These could be signs of a serious condition.

• nervousness, dizziness, or sleeplessness occurs

PREGNANCY OR BREAST FEEDING

If pregnant or breast-feeding, ask a health professional before use.

Keep out of reach of children.

In case of overdose, get medical help or contact a Poison Control Center right away. Quick medical attention is critical for adults as well as for children even if you do not notice any signs or symptoms.

Directions

• do not take more than the recommended dose

• adults and children 12 years and over: take 2 capsules with water every 4 hours. Do not exceed 10 capsules in 24 hours or as directed by a doctor.

• children under 12 years: do not use

Other Information

• store at room temperature. Avoid excessive heat above 40ºC (104ºF).

Inactive ingredients

D&C yellow no.10, FD&C blue no.1, gelatin, glycerin, mica, polyethylene glycol 400, povidone K 30, purified water, sorbitol sorbitan solution, titanium dioxide